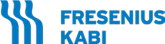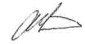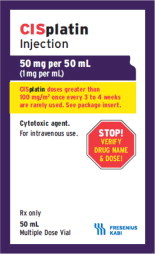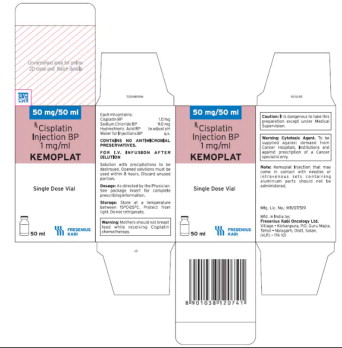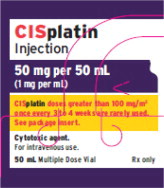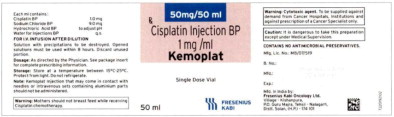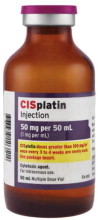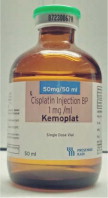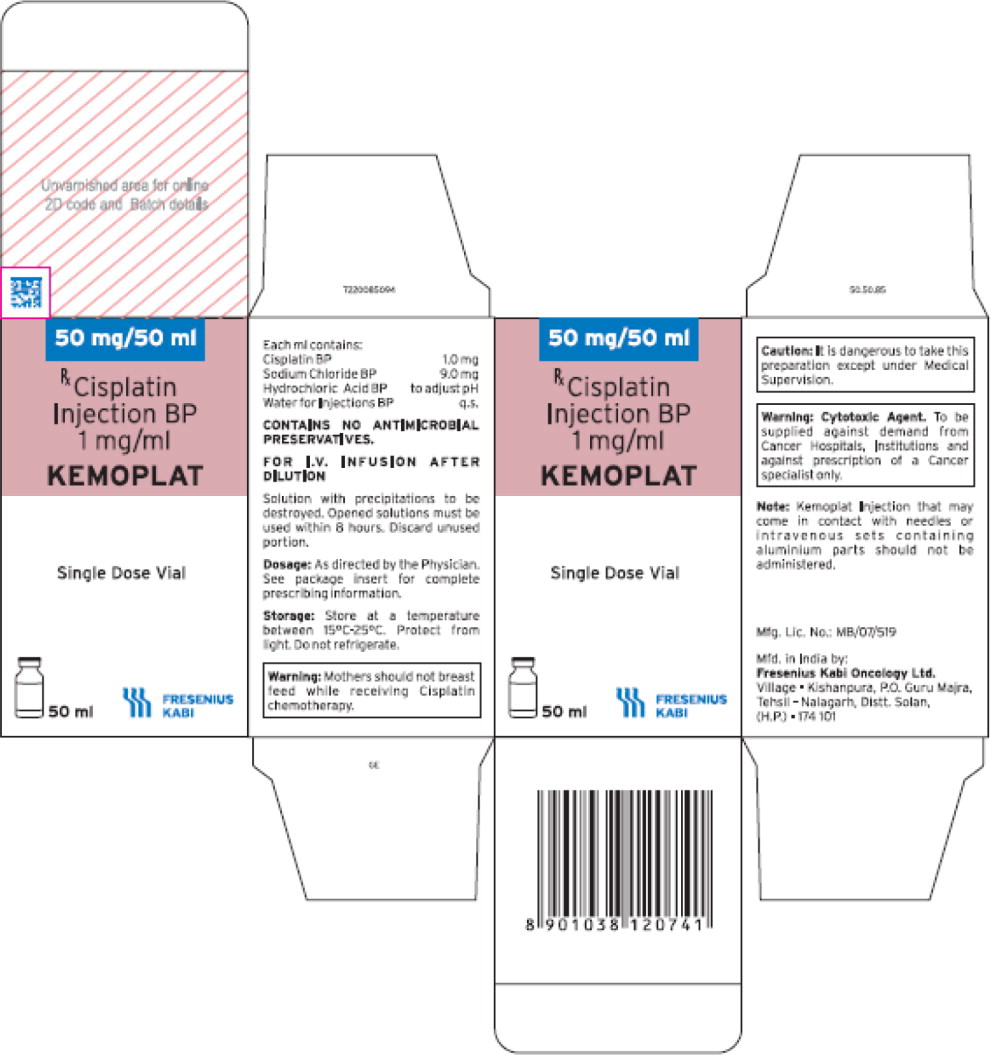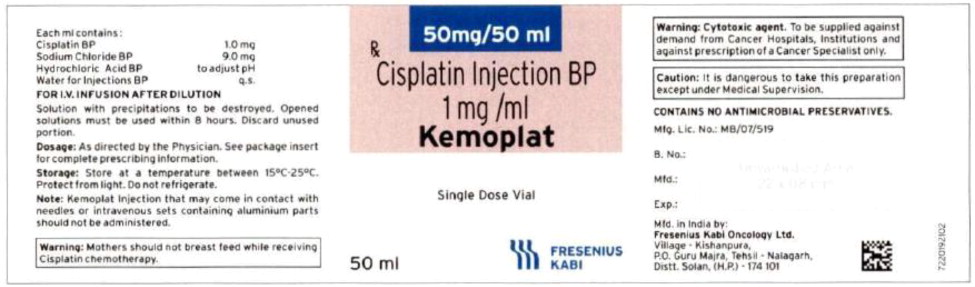 DRUG LABEL: Cisplatin
NDC: 65219-359 | Form: INJECTION, SOLUTION
Manufacturer: Fresenius Kabi USA, LLC
Category: prescription | Type: HUMAN PRESCRIPTION DRUG LABEL
Date: 20240223

ACTIVE INGREDIENTS: CISPLATIN 1 mg/1 mL
INACTIVE INGREDIENTS: SODIUM CHLORIDE; HYDROCHLORIC ACID; WATER

HEALTH CARE PROVIDER LETTER

Fresenius Kabi USA, LLC
Three Corporate Drive
Lake Zurich, Illinois 60047
T 847-550-2300
T 888-391-6300

August 30, 2023

www.fresenius-kabi.com/us

IMPORTANT PRESCRIBING INFORMATION

Subject: Temporary Importation of CISplatin Injection to Address Drug Shortage

Dear Healthcare Professional,

Due to the critical shortage of CISplatin Injection in the U.S. market, Fresenius Kabi USA, LLC (Fresenius Kabi USA) is coordinating with the U.S. Food and Drug Administration (FDA) to increase availability of the drug. Fresenius Kabi USA has initiated temporary importation of CISplatin Injection BP (KEMOPLAT) 50 mg/50 mL into the U.S. market. This product is marketed in Europe and is manufactured in India and is not FDA-approved.

At this time, no other entity except Fresenius Kabi USA is authorized by the FDA to import or distribute Fresenius Kabi's CISplatin Injection in the U.S.

Effective immediately, and during this temporary period, Fresenius Kabi USA will distribute the following presentation of CISplatin Injection to address the critical shortage:

Product Name | Quantity | Description | U.S. NDC Number | Lot Number | Exp Date
CISplatin Injection BP† (KEMOPLAT) 50 mg/50 mL (1 mg/mL) †BP = British Pharmacopeia | 1 amber single dose vial per carton | Clear, colorless to pale yellow solution. Each mL contains 1 mg Cisplatin and 9 mg sodium chloride in water for injection | 65219-359-50 | 87230281A | 05/2025

It is important to note the following:

- The imported product is labeled CISplatin Injection BP (KEMOPLAT) 50 mg/50 mL (1 mg/mL). BP stands for British Pharmacopeia and is not an acronym for an ingredient in the formulation. The BP provides quality standards for UK pharmaceutical substances and medicinal products.
- The carton labeling and container labeling do not include the warning statements, “Stop! Verify Drug Name and Dose!” or “CISplatin doses greater than 100 mg/m^2 once every 3 to 4 weeks are rarely used.” See U.S. package insert.
- The product is a single dose vial. Fresenius Kabi does NOT have extended stability data once the vial is punctured or information on withdrawing multiple doses.
- The imported product is a clear, colorless to pale yellow solution while the US product is a clear, colorless solution.
- Any barcodes on CISplatin Injection will not be appropriately recognized by scanning systems used in the United States and should NOT be used. Institutions should manually input the product into their systems to confirm that barcode systems do not provide incorrect information when the product is scanned. Alternative procedures should be followed to assure that the correct drug product is being prepared and administered to individual patients.
- In addition, the carton of the imported product does not include a product identifier as required under the Drug Supply Chain Security Act (DSCSA). Specifically, each package of product does not include the NDC, unique serial number, lot number, and expiration date in both human-readable form and a two-dimensional data matrix barcode.

Please ensure that staff and others within the institution who may be involved in the administration of CISplatin Injection receive a copy of this letter and review the information.

This communication and product information is available on the Fresenius Kabi USA website: https://www.fresenius-kabi.com/us/documents/CISplatin-DHCP-Letter.pdf as well as on the FDA Drug Shortage website http://www.fda.gov/Druqs/DruqSafetv/DruqShortaqes/default.htm.

REPORTING ADVERSE EVENTS

To report adverse events experienced with the use of this product, call Fresenius Kabi USA Vigilance at 1-800-551-7176, Monday - Friday, between the hours of 8 a.m. and 5 p.m. (CST), or e-mail adverse.events.USA@fresenius-kabi.com.

To report a product quality complaint with the use of this product, call 1-800-551-7176 or e-mail productcomplaint.USA@fresenius-kabi.com.

Fresenius Kabi USA CONTACT NUMBERS: Please use the following contact numbers as appropriate:

Reason To Call | Department | Number
ADE Reporting | Vigilance Department | 1-800-551-7176
Clinical/Technical Info. Or Product Quality Complaint | Medical Affairs Department | 1-800-551-7176
Product Availability & Ordering | Customer Service Department | 1-888-386-1300

Adverse reactions or quality problems experienced with the use of this product may be reported to the FDA's MedWatch Adverse Event Reporting program either online, by regular mail or by fax.

- Complete and submit the report Online: www.fda.gov/medwatch/report.htm
- Regular Mail or Fax: Download form http://www.fda.gov/medwatch/qetforms.htm or call 1-800-332-1088 to request a reporting form, then complete and return to the address on the pre-addressed form, or submit by fax to 1-800-FDA-0178 (1-800-332-0178).

Sincerely,

Anthony Giessert, Ph.D.
Vice President, Quality Assurance
Fresenius Kabi USA, LLC

CISplatin Injection Product Labels

U.S. FDA Approved Product

Imported Product†

Carton Label

Vial Label

Product Image

†BP = British Pharmacopeia

CISplatin Injection Product and Prescribing Information Side-by-Side Comparison Table

 | U.S. FDA Approved Product | Imported Product
Product Name | CISplatin Injection | CISplatin Injection BP (KEMOPLAT) (BP = British Pharmacopeia)
Active Ingredient | CISplatin | CISplatin
Available Strengths/Concentrations | 50 mg/50 mL (1 mg/mL) 100 mg/100 mL (1 mg/mL) 200 mg/200 mL (1 mg/mL) | 50 mg/50 mL (1 mg/mL)
Route of Administration | For Intravenous Use (must be further diluted prior to administration) | For I.V. Infusion After Dilution
Container | Amber multiple dose vial with 28 mm vial closure The container closure is not made with natural rubber latex. | Amber single dose vial with 20 mm vial closure The container closure is not made with natural rubber latex.
Product Description | Cisplatin Injection is a clear, colorless, sterile aqueous solution. Each 50 mL, 100 mL or 200 mL amber vial of Cisplatin Injection contains: 1 mg/mL cisplatin, 9 mg/mL sodium chloride, hydrochloric acid and/or sodium hydroxide to adjust pH, and water for injection to a final volume of 50 mL, 100 mL or 200 mL, respectively. The pH range of Cisplatin Injection is 3.8 to 5.9. | Kemoplat is a clear, colourless to pale yellow solution. KEMOPLAT is a sterile solution of Cisplatin BP 1.0mg/ml (50ml pack), sodium chloride BP 9mg/ml in Water for Injections BP.
Storage and Handling | Store at 20° to 25°C (68° to 77°F) [see USP Controlled Room Temperature]. Do not refrigerate. Protect from light. Stability Cisplatin is a sterile, multiple dose vial without preservatives. Store at 20° to 25°C (68° to 77°F) [see USP Controlled Room Temperature]. Do not refrigerate. Protect unopened container from light. The cisplatin remaining in the amber vial following initial entry is stable for 28 days protected from light or for 7 days under fluorescent room light. | Store at a temperature between 15°C - 25°C. Protect from light. Do not refrigerate.
Indications | Cisplatin Injection is indicated as therapy to be employed as follows: Metastatic Testicular Tumors In established combination therapy with other approved chemotherapeutic agents in patients with metastatic testicular tumors who have already received appropriate surgical and/or radiotherapeutic procedures. Metastatic Ovarian Tumors In established combination therapy with other approved chemotherapeutic agents in patients with meta static ovarian tumors who have already received appropriate surgical and/or radiotherapeutic procedures. An established combination consists of cisplatin and cyclophosphamide. Cisplatin Injection, as a single agent, is indicated as secondary therapy in patients with metastatic ovarian tumors refractory to standard chemotherapy who have not previously received Cisplatin Injection therapy. Advanced Bladder Cancer Cisplatin Injection is indicated as a single agent for patients with transitional cell bladder cancer which is no longer amenable to local treatments, such as surgery and/or radiotherapy. | KEMOPLAT is indicated for following indications: Metastatic Testicular Cancer: In established combination therapy with other approved chemotherapeutic agents in patients with metastatic testicular tumors who have already received appropriate surgical and/or radio therapeutic procedures. Metastatic Ovarian Cancer: In established combination therapy with other approved chemotherapeutic agents KEMOPLAT is used in patients with metastatic ovarian tumors who have already received appropriate surgical and/or radio therapeutic procedures. Also as a single agent, it is indicated as secondary therapy in patients with metastatic ovarian tumors refractory to standard chemotherapy who have not previously received cisplatin therapy. Advanced Bladder Cancer: Cisplatin is indicated as a single agent for patients with transitional cell bladder cancer, which is no longer amenable to local treatments such as surgery and/or radiotherapy.
Contraindications | Cisplatin is contraindicated in patients with pre-existing renal impairment. Cisplatin should not be employed in myelosuppressed patients, or in patients with hearing impairment. Cisplatin is contraindicated in patients with a history of allergic reactions to cisplatin or other platinum-containing compounds. | Use of cisplatin is contraindicated in patients with a history of hypersensitivity to cisplatin or other platinum containing compounds. Cisplatin should not be used in patients with preexisting renal impairment, myelosuppressed patients or patients with hearing impairment.
Dosage and Administration | Cisplatin is administered by slow intravenous infusion. CISPLATIN SHOULD NOT BE GIVEN BY RAPID INTRAVENOUS INJECTION. Note: Needles or intravenous sets containing aluminum parts that may come in contact with cisplatin should not be used for preparation or administration. Aluminum reacts with cisplatin, causing precipitate formation and a loss of potency. Metastatic Testicular Tumors The usual cisplatin dose for the treatment of testicular cancer in combination with other approved chemo therapeutic agents is 20 mg/m^2 IV daily for 5 days per cycle. Metastatic Ovarian Tumors The usual cisplatin dose for the treatment of metastatic ovarian tumors in combination with cyclophosphamide is 75 to 100 mg/m^2 IV per cycle once every 4 weeks (DAY 1). The dose of cyclophosphamide when used in combination with cisplatin is 600 mg/m^2 IV once every 4 weeks (DAY 1). For directions for the administration of cyclo-phosphamide, refer to the cyclophosphamide package insert. In combination therapy, cisplatin and cyclophosphamide are administered sequentially. As a single agent, cisplatin should be administered at a dose of 100 mg/m^2 IV per cycle once every 4 weeks. Advanced Bladder Cancer Cisplatin should be administered as a single agent at a dose of 50 to 70 mg/m^2 IV per cycle once every 3 to 4 weeks depending on the extent of prior exposure to radiation therapy and/or prior chemotherapy. For heavily pre-treated patients an initial dose of 50 mg/m^2 per cycle repeated every 4 weeks is recommended. All Patients Pretreatment hydration with 1 to 2 liters of fluid infused for 8 to 12 hours prior to a cisplatin dose is recommended. The drug is then diluted in 2 liters of 5% Dextrose in 1/2 or 1/3 normal saline containing 37.5 g of mannitol, and infused over a 6- to 8-hour period. If diluted solution is not to be used within 6 hours, protect solution from light. Do not dilute cisplatin in just 5% Dextrose Injection. Adequate hydration and urinary output must be maintained during the following 24 hours. A repeat course of cisplatin should not be given until the serum creatinine is below 1.5 mg/100 mL, and/or the BUN is below 25 mg/100 mL. A repeat course should not be given until circulating blood elements are at an acceptable level (platelets ≥100,000/mm^3, WBC ≥4,000/mm^3). Subsequent doses of cisplatin should not be given until an audiometric analysis indicates that auditory acuity is within normal limits. Preparation of Intravenous Solutions The aqueous solution should be used intravenously only and should be administered by IV infusion over a 6- to 8-hour period (see DOSAGE AND ADMINISTRATION). Parenteral drug products should be inspected visually for particulate matter and discoloration prior to administration, whenever solution and container permit. NOTE TO PHARMACIST: Exercise caution to prevent inadvertent cisplatin overdosage. Please call prescriber if dose is greater than 100 mg/m^2 per cycle. Aluminum and flip-off seal of vial have been imprinted with the following statement: CALL DR. IF DOSE >100 MG/M^2/CYCLE. | Metastatic Testicular Cancer: The usual dose for the treatment of testicular cancer in combination with other approved chemotherapeutic agents is 20 mg/m^2 I.V. daily for 5 days per cycle. Metastatic Ovarian Cancer: The usual cisplatin dose for the treatment of metastatic ovarian cancer in combination with cyclophosphamide is 75-100 mg/m^2 I.V. per cycle once every 4 weeks, (Day 1). As a single agent cisplatin should be administered as 100 mg/m^2/cycle IV every 4 weeks. Advanced Bladder Cancer: cisplatin should be administered as a single agent at a dose of 50-70 mg/m^2 I.V. per cycle once every 3 to 4 weeks depending on the extent of prior exposure to radiation therapy and/or prior chemotherapy. For heavily pretreated patients an initial dose of 50 mg/m^2 per cycle repeated every four weeks is recommended. a) Pre Treatment Hydration: Patients should be adequately hydrated before and for 24 hrs. after KEMOPLAT administration in order to induce diuresis and minimize nephrotoxicity. Hydration may be achieved either by I.V. infusion of 2 liters of 0.9% sodium chloride or dextrose saline (Dextrose 5% in one fifth normal saline (0.18% Sodium chloride injection) over a 6-12 hr. period. During the last 30 minutes of the pre treatment hydration or after the hydration, 375 ml of 20% mannitol injection may be administered via a side arm drip. b) Preparation of KEMOPLAT infusion: KEMOPLAT should be added to 2 liters of 0.9% sodium chloride injection or Dextrose-Saline solution. c) Treatment: Following pre-hydration, KEMOPLAT infusion is administered over 1-2 hrs. A longer infusion time of 6-8 hrs may decrease gastrointestinal and renal toxicities. d) Post Treatment Hydration It is recommended that I.V. hydration should continue after treatment with administration of 2 liters 0.9% sodium chloride IV infusion or Dextrose-saline over a period of 6-12 hours. NOTE: Since aluminum reacts with and inactivates cisplatin, it is important not to use needles or other equipment that contain aluminum while preparing or administering KEMOPLAT.

PACKAGE LABEL

PACKAGE LABEL – PRINCIPAL DISPLAY PANEL – Cisplatin Injection 50 mL Carton Panel

50mg/50 ml

Rx

Cisplatin

Injection BP

1 mg/ml

KEMOPLAT

Single Dose Vial

50 ml

PACKAGE LABEL

PACKAGE LABEL – PRINCIPAL DISPLAY PANEL – Cisplatin Injection 50 mL Vial Label

50mg/50 ml

Rx

Cisplatin Injection BP

1 mg /ml

Kemoplat

Single Dose Vial

50 ml